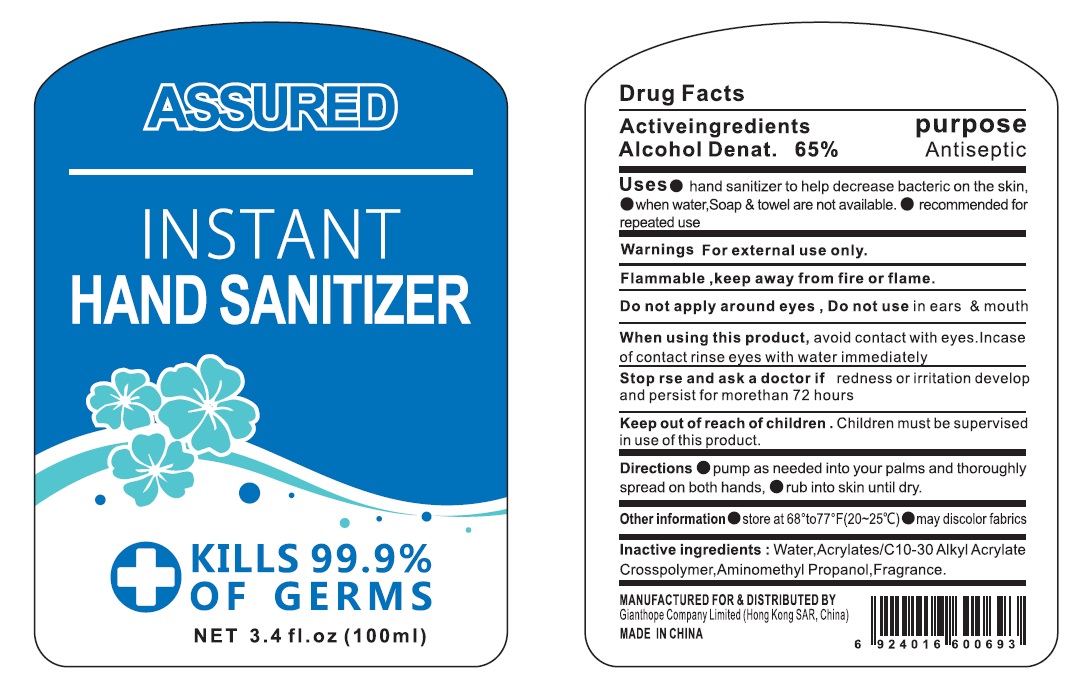 DRUG LABEL: Assured Instant Hand Sanitizer
NDC: 78524-002 | Form: GEL
Manufacturer: Gianthope Arts Product (Huizhou) Company Limited
Category: otc | Type: HUMAN OTC DRUG LABEL
Date: 20200602

ACTIVE INGREDIENTS: ALCOHOL 65 mL/100 mL
INACTIVE INGREDIENTS: WATER; GLYCERIN; CARBOMER COPOLYMER TYPE A; AMINOMETHYLPROPANOL

Active ingredient

Ethyl Alcohol 65%

Purpose

Antiseptic

Use

- Hand sanitizer to help decrease bacteria on the skin
- when water, soap & towel are not available
- Recommended for repeated use.

Warnings

For external use only.

Flammable,

Keep away from fire or flame

Do not apply around eyes, do not use in ears and mouth.

When using this product

avoid contact with eyes. In case of contact, rinse eyes with water immediately

Stop use and ask a doctor if

redness or irritation develop and persist for more than 72 hours

Keep out of reach of children.

Children must be supervised in use of this product.

Directions

- Pump as needed into your palms and thoroughly spread on both hands
- Rub into skin until dry.

Inactive ingredients

Water, Acrylates/C10-30 Alkyl Acrylate Crosspolymer, Aminomethyl Propanol, Fragrance

Other information

- Store between 68-77℉ (20-25℃)
- May discolor fabrics.